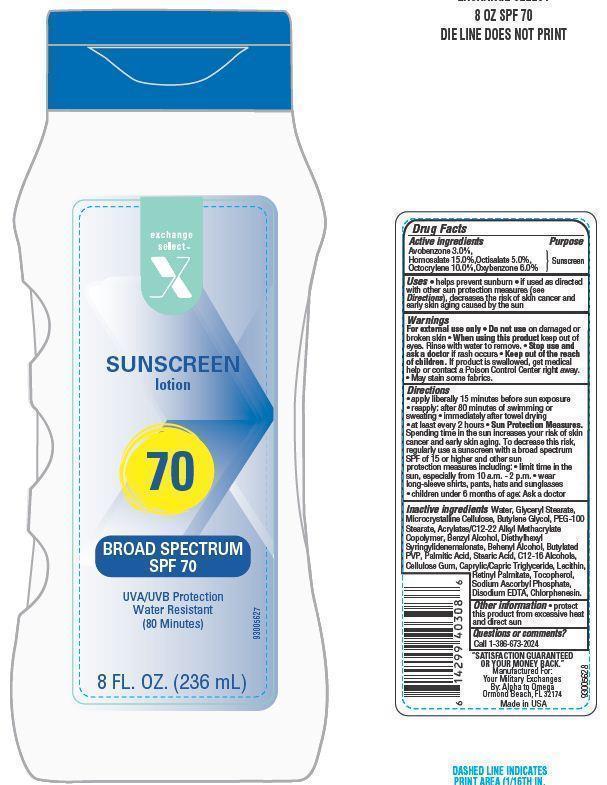 DRUG LABEL: Exchange Select Sunscreen
NDC: 55301-013 | Form: LOTION
Manufacturer: ARMY AND AIR FORCE EXCHANGE SERVICE
Category: otc | Type: HUMAN OTC DRUG LABEL
Date: 20131024

ACTIVE INGREDIENTS: AVOBENZONE 3 g/100 g; HOMOSALATE 15 g/100 g; OCTISALATE 5 g/100 g; OCTOCRYLENE 10 g/100 g; OXYBENZONE 6 g/100 g
INACTIVE INGREDIENTS: WATER; GLYCERYL MONOSTEARATE; STEARIC ACID; CELLULOSE, MICROCRYSTALLINE; BUTYLENE GLYCOL; PEG-100 STEARATE; BENZYL ALCOHOL; DIETHYLHEXYL SYRINGYLIDENEMALONATE; DOCOSANOL; TOCOPHEROL; EDETATE DISODIUM; PALMITIC ACID; CARBOXYMETHYLCELLULOSE SODIUM; MYRISTYL ALCOHOL; TRICAPRYLIN; VITAMIN A PALMITATE; SODIUM ASCORBYL PHOSPHATE; CETYL ALCOHOL; LAURYL ALCOHOL; CHLORPHENESIN

Drug Facts

Active ingredients

Avobenzone 3.0 %

Homosalate 15.0%

Octisalate 5.0%

Octocrylene 10.0%

Oxybenzone 6.0%

Purpose

Sunscreen

Uses

- helps prevent sunburn
- If used as directed with other sun protection measures(see Directions), decreases the risk of skin cancer and early skin

Warnings

For external use only. Do not use on damaged or broken skin.

When using this product

- keep out of eyes. Rinse with water to remove.

Stop use and ask a doctor if

- rash occurs.

Keep out of reach of children

If swallowed, get medical help or contact a Poison Control Center right away.

- May stain some fabrics.

Directions

- apply liberally 15 minutes before sun exposure
- reapply:
- after 80 minutes of swimming or sweating
- immediately after towel drying
- at least every 2 hours
- Sun Protection Measures. Spending time in the sun increases your risk of skin cancer and early skin aging. To decrease this risk,regularly use a sunscreen with a broad spectrum SPF of 15 or higher and other sun protection measures including:
- limit time in the sun, especially from 10 a.m. - 2 p.m.
- wear long-sleeve shirts, pants,hats and sunglasses
- children under 6 months of age: Ask a doctor

Other information

- protect this product from excessive heat and direct sun

Inactive ingredients

Water, Glyceryl Stearate, Microcrystalline Cellulose, Butylene Glycol, PEG-100 Stearate, Acrylates/C12-22 Alkyl Methacrylate Copolymer, Benzyl Alcohol, Diethylhexyl Syringylidenemalonate, Behenyl Alcohol, Butylated PVP, Palmitic Acid, Stearic Acid, C12-16 Alcohols, Cellulose Gum, Caprylic/Capric Triglyceride, Lecithin, Retinyl Palmitate, Tocopherol, Sodium Ascorbyl Phosphate, Disodium EDTA, Chlorphenesin.

Principal Display Panel

exchange

select

X

SUNSCREEN

lotion

70

BROAD SPECTRUM SPF 70

UVA/UVB Protection

Water Resistant

(80 Minutes)

8 FL. OZ. (236 mL)

Questions or comments?

Call 1-386-673-2024